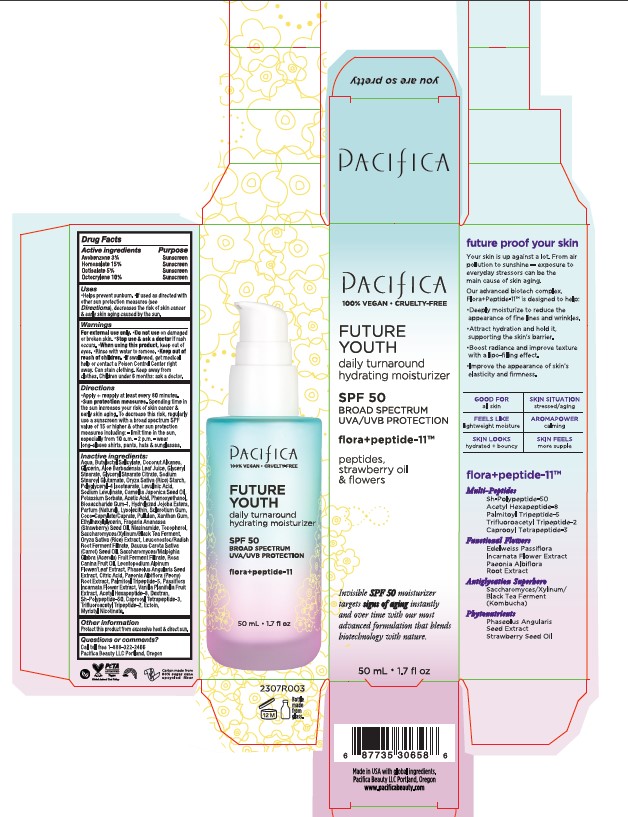 DRUG LABEL: Future Youth Daily Turnaround Hydrating Moisturizer SPF 50
NDC: 61197-219 | Form: CREAM
Manufacturer: Pacifica Beauty, LLC
Category: otc | Type: HUMAN OTC DRUG LABEL
Date: 20250103

ACTIVE INGREDIENTS: OCTISALATE 5 g/100 mL; HOMOSALATE 15 g/100 mL; AVOBENZONE 3 g/100 mL; OCTOCRYLENE 10 g/100 mL
INACTIVE INGREDIENTS: COCONUT ALKANES; LEVULINIC ACID; HYDROLYZED JOJOBA ESTERS (ACID FORM); ADZUKI BEAN; ECTOINE; MALPIGHIA GLABRA FRUIT; COCO-CAPRYLATE/CAPRATE; NIACINAMIDE; RICE GERM; ROSA CANINA FRUIT OIL; PASSIFLORA INCARNATA FLOWER; GLYCERIN; POTASSIUM SORBATE; XANTHAN GUM; SODIUM STEAROYL GLUTAMATE; LEUCONOSTOC/RADISH ROOT FERMENT FILTRATE; CARROT SEED OIL; WATER; GLYCERYL MONOSTEARATE; GLYCERYL STEARATE CITRATE; SODIUM LEVULINATE; CAMELLIA JAPONICA SEED OIL; BIOSACCHARIDE GUM-1; PULLULAN; PAEONIA LACTIFLORA ROOT; VANILLA; STARCH, RICE; POLYGLYCERYL-4 ISOSTEARATE; ACETIC ACID; PHENOXYETHANOL; ETHYLHEXYLGLYCERIN; STRAWBERRY SEED OIL; LEONTOPODIUM ALPINUM FLOWERING TOP; PALMITOYL TRIPEPTIDE-5; ACETYL HEXAPEPTIDE-8; DEXTRAN 40; CAPROOYL TETRAPEPTIDE-3; ALOE VERA LEAF; TRIFLUOROACETYL TRIPEPTIDE-2; MYRISTYL NICOTINATE; BUTYLOCTYL SALICYLATE; CITRIC ACID MONOHYDRATE; ELASTIN (HUMAN); TOCOPHEROL; BETASIZOFIRAN

Future Youth Daily Turnaround Hydrating Moisturizer SPF 50

Active Ingredients

Active ingredients Purpose

Avobenzone 3% Sunscreen

Homosalate 15% Sunscreen

Octisalate 5% Sunscreen

Uses

Helps prevent sunburn. If used as directed with other sun protection measures (see Directions), decreases the risk of skin cancer & early skin aging caused by the sun.

Indications & Usage

Uses

Helps prevent sunburn.

Warnings

For external use only. Do not use on damaged or broken skin. Stop use & ask a doctor if rash occurs. When using this product, keep out of eyes. Rinse with water to remove. Keep out of reach of children. If swallowed, get medical help or contact a Poison Control Center right away. Can stain clothing. Keep away from clothes. Children under 6 months: ask a doctor.

Directions

Apply + reapply at least every 80 minutes. Sun protection measures. Spending time in the sun increases your risk of skin cancer & early skin aging. To decrease this risk, regularly use a sunscreen with a broad spectrum SPF value of 15 or higher & other sun protection measures including: limit time in the sun, especially from 10 a.m. - 2 p.m. - wear long-sleeve shirts, pants, hats & sunglasses.

Keep Out of Reach of Children

Warnings

Keep out of reach of children.

Inactive Ingredients

Aqua, Butyloctyl Salicylate, Coconut Alkanes, Glycerin, Aloe Barbadensis Leaf Juice, Glyceryl Stearate, Glyceryl Stearate Citrate, Sodium Stearoyl Glutamate, Oryza Sativa (Rice) Starch, Polyglyceryl-4 Isostearate, Levulinic Acid, Sodium Levulinate, Camellia Japonica Seed Oil, Potassium Sorbate, Acetic Acid, Phenoxyethanol, Biosaccharide Gum-1, Hydrolyzed Jojoba Esters, Parfum (Natural), Lysolecithin, Sclerotium Gum, Coco-Caprylate/Caprate, Pullulan, Xanthan Gum, Ethylhexylglycerin, Fragaria Ananassa (Strawberry) Seed Oil, Niacinamide, Tocopherol, Saccharomyces/Xylinum/Black Tea Ferment, Oryz Sativa (Rice) Extract, Leuconostoc/Radish Root Ferment Filtrate, Daucus Carota Sativa (Carrot) Seed Oil, Saccharomyces/Malpighia Glabra (Acerola) Fruit Ferment Filtrate, Rosa Canina Fruit Oil, Leontopodium Alpinum Flower/Leaf Extract, Paseolus Angularis Seed Extract, Citric Acid, Paeonia Albiflora (Peony) Root Extract, Palmitoyl Tripeptide-5, Passiflora Incarnata Flower Extract, Vanilla Planifolia Fruit Extract, Acetyl Hexapeptide-8, Dextran, Sh-Polypeptide-50, Caprooyl Tetrapeptide-3, Trifluoroacetyl Tripeptide-2, Ectoin, Myristyl Nicotinate.

Other Information

Protect this product from excessive heat & direct sun.

Questions or Comments

Call toll free 1-888-322-2466

Pacifica Beauty LLC Portland, Oregon